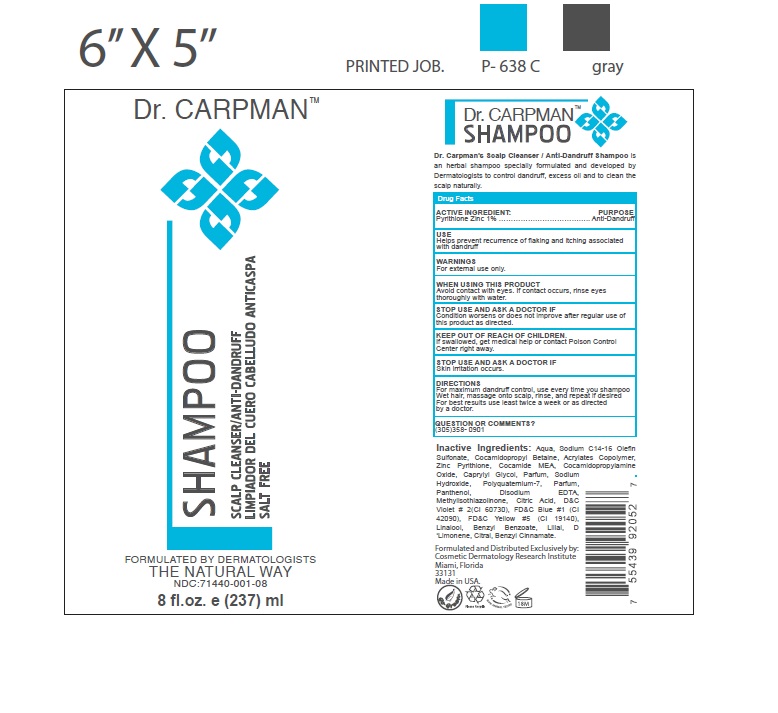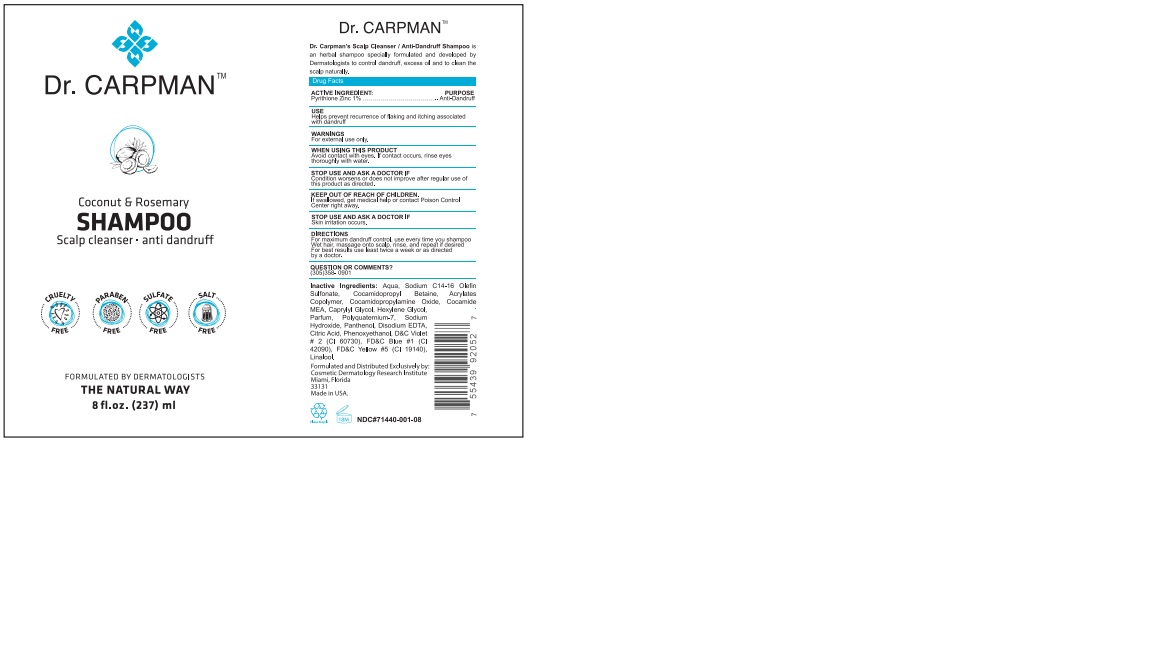 DRUG LABEL: Pyrithione Zinc
NDC: 71440-001 | Form: SHAMPOO
Manufacturer: Cosmetic Dermatology Research Institute, LLC.
Category: otc | Type: HUMAN OTC DRUG LABEL
Date: 20241112

ACTIVE INGREDIENTS: PYRITHIONE ZINC 2.41 g/237 mL
INACTIVE INGREDIENTS: PANTHENOL; FD&C BLUE NO. 1; FD&C YELLOW NO. 5; HEXYLENE GLYCOL; D&C VIOLET NO. 2; WATER; SODIUM HYDROXIDE; POLYQUATERNIUM-7 (70/30 ACRYLAMIDE/DADMAC; 1600000 MW); LINALOOL, (+)-; CAPRYLYL GLYCOL; SODIUM C14-16 OLEFIN SULFONATE; COCAMIDE; PHENOXYETHANOL

71440-001-08